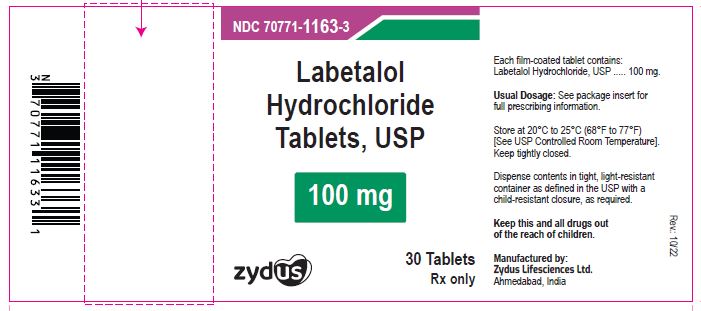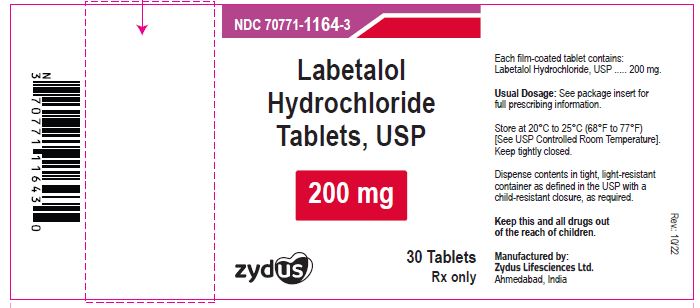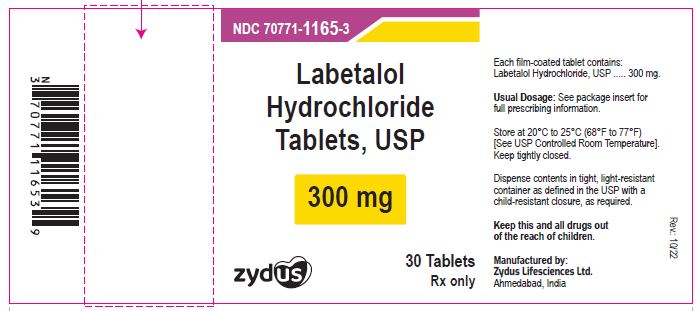 DRUG LABEL: Labetalol Hydrochloride
NDC: 70771-1163 | Form: TABLET, FILM COATED
Manufacturer: Zydus Lifesciences Limited
Category: prescription | Type: HUMAN PRESCRIPTION DRUG LABEL
Date: 20241130

ACTIVE INGREDIENTS: LABETALOL HYDROCHLORIDE 100 mg/1 1
INACTIVE INGREDIENTS: ALUMINUM OXIDE; D&C YELLOW NO. 10; FERRIC OXIDE RED; FERRIC OXIDE YELLOW; HYPROMELLOSES; LACTOSE MONOHYDRATE; MAGNESIUM STEARATE; POLYETHYLENE GLYCOL, UNSPECIFIED; SODIUM STARCH GLYCOLATE TYPE A POTATO; STARCH, CORN; TALC; TITANIUM DIOXIDE

Labetalol Hydrochloride Tablets, USP
Rx only

PACKAGE LABEL.PRINCIPAL DISPLAY PANEL

NDC 70771-1163-3

Labetalol hydrochloride tablets, 100 mg

Rx only

30 tablets

NDC 70771-1164-3

Labetalol hydrochloride tablets, 200 mg

Rx only

30 tablets

NDC 70771-1165-3

Labetalol hydrochloride tablets, 300 mg

Rx only

30 tablets